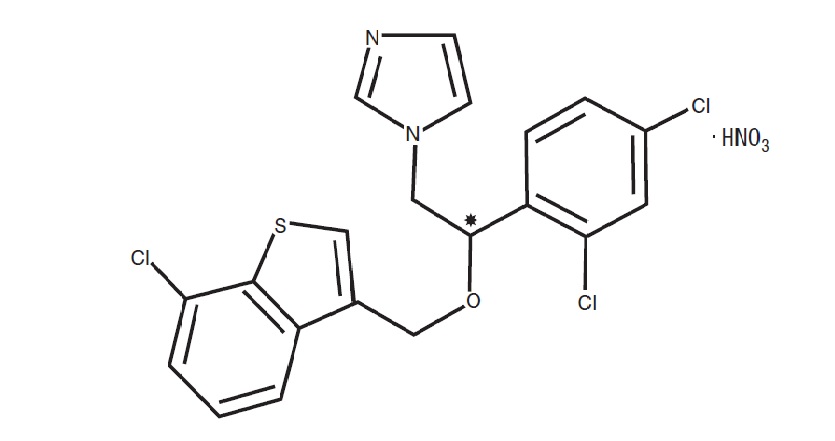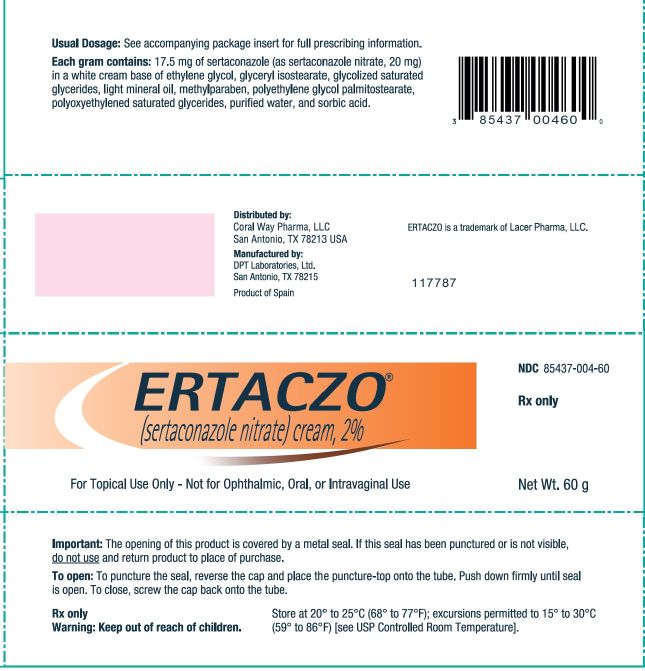 DRUG LABEL: Ertaczo
NDC: 85437-004 | Form: CREAM
Manufacturer: Coral Way Pharma, LLC
Category: prescription | Type: HUMAN PRESCRIPTION DRUG LABEL
Date: 20251107

ACTIVE INGREDIENTS: SERTACONAZOLE NITRATE 20 mg/1 g
INACTIVE INGREDIENTS: ETHYLENE GLYCOL; GLYCERYL ISOSTEARATE; LIGHT MINERAL OIL; METHYLPARABEN; SORBIC ACID; PEG-6 STEARATE; GLYCOL STEARATE; PEG-32 STEARATE; WATER

HIGHLIGHTS OF PRESCRIBING INFORMATION

These highlights do not include all the information needed to use ERTACZO Cream safely and effectively. See full prescribing information for ERTACZO Cream.
ERTACZO®(sertaconazole nitrate) cream, for topical use
Initial U.S. Approval: 2003

1 INDICATIONS AND USAGE

ERTACZO cream, 2% is an azole antifungal indicated for the topical treatment of interdigital tinea pedis in immunocompetent adult and pediatric patients 12 years of age and older caused by Trichophyton rubrum, Trichophyton mentagrophytes, and Epidermophyton floccosum. (1)

2 DOSAGE AND ADMINISTRATION

- Apply ERTACZO cream, 2% to the affected and immediate surrounding area(s) twice daily for 4 weeks. (2)
- Not for ophthalmic, oral, or intravaginal use. (2)

3 DOSAGE FORMS AND STRENGTHS

Cream, 2%. (3)

4 CONTRAINDICATIONS

None. (4)

6 ADVERSE REACTIONS

Most common adverse reactions observed in clinical trials (incidence >2%) were contact dermatitis, dry skin, burning skin, application site skin tenderness. (6.1)

To report SUSPECTED ADVERSE REACTIONS, contact Coral Way Pharma, LLC at 1-210-641-5334 or FDA at 1-800-FDA-1088 or www.fda.gov/medwatch.

FULL PRESCRIBING INFORMATION

1 INDICATIONS AND USAGE

ERTACZO®cream, 2%, is indicated for the topical treatment of interdigital tinea pedis in immunocompetent adult and pediatric patients 12 years of age and older caused by Trichophyton rubrum, Trichophyton mentagrophytes,and Epidermophyton floccosum.

2 DOSAGE AND ADMINISTRATION

- Apply ERTACZO cream, 2% twice daily for 4 weeks. Apply a sufficient amount of ERTACZO cream, 2% to cover both the affected areas between the toes and the immediately surrounding healthy skin.
- Use ERTACZO cream, 2% for the full treatment time recommended by the physician, even though symptoms may have improved.
- Dry the affected area(s) thoroughly before application, if using ERTACZO cream, 2% after bathing.
- Wash hands after use.
- Avoid the use of occlusive dressings or wrappings.
- For topical use.
- Not for ophthalmic, oral, or intravaginal use.

3 DOSAGE FORMS AND STRENGTHS

Cream, 2%. Each gram of ERTACZO cream, 2%, contains 17.5 mg of sertaconazole (as sertaconazole nitrate, 20 mg) in a white cream base.

4 CONTRAINDICATIONS

None.

5 WARNINGS AND PRECAUTIONS

5.1 Local Adverse Reactions

If irritation develops, discontinue treatment and institute appropriate therapy.

Physicians should exercise caution when prescribing ERTACZO cream, 2%, to patients known to be sensitive to azole antifungals since cross-reactivity may occur.

6 ADVERSE REACTIONS

6.1 Clinical Trials Experience

Because clinical trials are conducted under widely varying conditions, adverse reaction rates observed in the clinical trials of a drug cannot be directly compared to rates in the clinical trials of another drug and may not reflect the rates observed in practice.

In clinical trials, cutaneous adverse events occurred in 7 of 297 (2%) subjects (2 of them severe) receiving ERTACZO cream, 2%, and in 7 of 291 (2%) subjects (2 of them severe) receiving vehicle. These reported cutaneous adverse events included contact dermatitis, dry skin, burning skin, and application site skin tenderness.

In a dermal sensitization trial, 8 of 202 evaluable subjects tested with ERTACZO cream, 2%, and 4 of 202 evaluable subjects tested with vehicle exhibited a erythematous reaction in the challenge phase. There was no evidence of cumulative irritation or contact sensitization in a repeated insult patch test involving 202 healthy volunteers.

6.2 Postmarketing Experience

The following adverse reactions have been identified during post-approval use of ERTACZO cream, 2%. Because these reactions are reported voluntarily from a population of uncertain size, it is not always possible to reliably estimate their frequency or establish a causal relationship to drug exposure.

Cutaneous adverse events:erythema, pruritus, vesiculation, desquamation, and hyperpigmentation.

8 USE IN SPECIFIC POPULATIONS

8.1 Pregnancy

Risk Summary

There are no available data on ERTACZO cream, 2% use in pregnant women to evaluate for a drug-associated risk of major birth defects, miscarriage, or adverse maternal or fetal outcomes. In animal reproduction studies, there were no adverse developmental effects observed with oral administration of sertaconazole nitrate to pregnant rats and rabbits during organogenesis at doses 40 and 80 times, respectively, the maximum recommended human dose (MRHD) based on body surface area (BSA) comparison. In rats, when maternal dosing was continued until weaning, a reduction in live birth indices and an increase in the number of still-born pups was observed at doses 20 and 40 times the MRHD based on BSA comparison (see Data).

The background risk of major birth defects and miscarriage for the indicated population is unknown. All pregnancies have a background risk of major birth defects, loss and other adverse outcomes. In the U.S. general population, the estimated background risk of major birth defects and miscarriage in clinically recognized pregnancies is 2-4% and 15-20%, respectively.

Data

Animal Data

Animal embryofetal development studies have not been conducted with ERTACZO cream, 2%. Embryofetal development studies performed in pregnant rats and rabbits administered oral doses of sertaconzaole nitrate up to 160 mg/kg/day (40 times [rats] and 80 times [rabbits] the MRHD based on a BSA comparison) during the period of organogenesis revealed no malformations or embryofetal developmental toxicity. In a pre- and postnatal development study, pregnant rats were administered oral doses of sertaconazole nitrate from pregnancy day 6 to lactation day 20. A reduction in live birth indices and an increase in the number of still-born pups were seen at doses 20 and 40 times the MRHD based on BSA comparison.

8.2 Lactation

Risk Summary

There are no data available on the presence of sertaconazole in human or animal milk, its effects on the breastfed infant, or its effects on milk production. The developmental and health benefits of breastfeeding should be considered along with the mother’s clinical need for ERTACZO cream, 2% and any potential adverse effects on the breastfed infant from ERTACZO cream, 2% or from the underlying maternal condition.

8.4 Pediatric Use

The safety and effectiveness of ERTACZO cream, 2%, have not been established in pediatric patients younger than 12 years of age.

8.5 Geriatric Use

Clinical trials of ERTACZO cream, 2%, did not include sufficient numbers of subjects aged 65 and over to determine whether they respond differently from younger subjects.

11 DESCRIPTION

ERTACZO (sertaconazole nitrate) cream, 2%, is for topical application. It contains the azole antifungal, sertaconazole nitrate. Sertaconazole nitrate contains one asymmetric carbon atom and exists as a racemic mixture of equal amounts of R and S enantiomers.

Sertaconazole nitrate is designated chemically as (±)-1-[2,4-dichloro-β-[(7-chlorobenzo-[ b]thien-3-yl)methoxy]phenethyl]imidazole nitrate. It has a molecular weight of 500.8. The molecular formula is C20H15Cl3N2OS ● HNO3, and the structural formula is as follows:

Sertaconazole nitrate is a white or almost white powder. It is practically insoluble in water, soluble in methanol, and sparingly soluble in alcohol and in methylene chloride. Each gram of ERTACZO cream, 2%, contains 17.5 mg of sertaconazole (as sertaconazole nitrate, 20 mg) in a white cream base of ethylene glycol, glyceryl isostearate, glycolized saturated glycerides, light mineral oil, methylparaben, polyethylene glycol palmitostearate, polyoxyethylened saturated glycerides, purified water, and sorbic acid.

12 CLINICAL PHARMACOLOGY

12.1 Mechanism of Action

Sertaconazole nitrate is an azole antifungal [see Clinical Pharmacology (12.4)] .

12.2 Pharmacokinetics

In a multiple-dose pharmacokinetic trial that included 5 male subjects with interdigital tinea pedis (range of diseased area, 42 - 140 cm^2; mean, 93 cm^2), ERTACZO cream, 2%, was topically applied every 12 hours for a total of 13 doses to the diseased skin (0.5 g sertaconazole nitrate per 100 cm^2). Sertaconazole concentrations in plasma measured by serial blood sampling for 72 hours after the thirteenth dose were below the limit of quantitation (2.5 ng/mL) of the analytical method used.

12.3 Microbiology

Mechanism of Action

Sertaconazole, an azole antifungal agent, inhibits fungal cytochrome P-450-mediated 14 alpha-lanosterol demethylase enzyme. This enzyme functions to convert lanosterol to ergosterol. Ergosterol is a key component of fungal cell membranes and lack of this component leads to fungal cell injury by leakage of key constituents in the cytoplasm from the cell.

Activity In Vitro and in Clinical Infections

Sertaconazole nitrate has been shown to be active against isolates of the following microorganisms in clinical infections [see Indications and Usage (1)] :

- Trichophyton rubrum
- Trichophyton mentagrophytes
- Epidermophyton floccosum

13 NONCLINICAL TOXICOLOGY

13.1 Carcinogenesis, Mutagenesis, Impairment of Fertility

In a 2-year rat dermal carcinogenicity study, topical administration of sertaconazole nitrate cream did not increase the number of neoplastic lesions compared to control animals, at sertaconazole nitrate doses of up to 800 mg/kg/day (200 times the MRHD based on a BSA comparison).

No clastogenic potential was observed in a mouse micronucleus test. Sertaconazole nitrate was nonclastogenic in the in vivo mouse sister chromatid exchange assay. There was no evidence that sertaconazole nitrate induced unscheduled DNA synthesis in primary rat hepatocyte cultures.

Rats treated orally with up to 160 mg/kg/day of sertaconazole nitrate (40 times the MRHD based on a BSA comparison), exhibited no toxicity or adverse effects on reproductive performance or fertility in male or female rats.

14 CLINICAL STUDIES

In two randomized, double-blind clinical trials, subjects 12 years and older with interdigital tinea pedis applied either ERTACZO cream, 2%, or vehicle, twice daily for 4 weeks. Subjects with moccasin-type (plantar) tinea pedis and/or onychomycosis were excluded from the trial. Two weeks after completion of therapy (6 weeks after beginning therapy), subjects were evaluated for signs and symptoms related to interdigital tinea pedis.

Treatment outcomes are summarized in the table below.

Treatment Outcomes as Percent (%) of Total Subjects with Interdigital Tinea Pedis
 | Trial 1 |  | Trial 2
 | Sertaconazole | Vehicle | Sertaconazole | Vehicle
Complete Cure*(Primary Efficacy Variable) | 13/99 (13.1%) | 3/92 (3.3%) | 28/103 (27.2%) | 5/103 (4.9%)
Effective Treatment** | 32/99 (32.3%) | 11/92 (12.0%) | 52/103 (50.5%) | 16/103 (15.5%)
Mycological Cure*** | 49/99 (49.5%) | 18/92 (19.6%) | 71/103 (68.9%) | 20/103 (19.4%)

*Complete Cure – Patients who had complete clearing of signs and symptoms and Mycological Cure.
**Effective Treatment – Patients who had minimal residual signs and symptoms of interdigital tinea pedis and Mycological Cure.
***Mycological Cure – Patients who had both negative microscopic KOH preparation and negative fungal culture.

In clinical trials, complete cure in ERTACZO cream, 2%-treated subjects was achieved in 32 of 160 (20%) subjects with Trichophyton rubrum, in 7 of 28 (25%) subjects with Trichophyton mentagrophytes, and in 1 of 13 (15%) subjects with Epidermophyton floccosum.

16 HOW SUPPLIED/STORAGE AND HANDLING

ERTACZO cream, 2%, is white in color and supplied in tubes in the following size:

60-gram tube NDC 85437-004-60

Store at 20° to 25°C (68° to 77°F); excursions permitted to 15° to 30°C (59° to 86°F) [see USP Controlled Room Temperature].

17 PATIENT COUNSELING INFORMATION

Advise the patient to read the FDA-approved patient labeling (Patient Information).

Instruct the patient of the following:

Administration Instructions

- ERTACZO cream, 2% is for topical use only.
- Avoid contact with the eyes, mouth, vagina, and other mucous membranes.
- Dry the affected area(s) thoroughly before application, if using ERTACZO cream, 2% after bathing.
- Wash hands after use.
- Use the medication for the full treatment time recommended by the physician, even though symptoms may have improved.
- Avoid the use of occlusive dressings unless otherwise directed by the physician [see Dosage and Administration (2)] .

Local Adverse Reactions

- Inform the physician if the area of application shows signs of increased irritation, redness, itching, burning, blistering, swelling, or oozing [see Warnings and Precautions (5.1)] .

Distributed by:
Coral Way Pharma, LLC
San Antonio, TX 78213 USA
Manufactured by:
DPT Laboratories, Ltd.
San Antonio, TX 78215
ERTACZO is a trademark of Lacer Pharma, LLC
141379

Patient Package Insert

PATIENT INFORMATION

ERTACZO® (er-tack-zo)

(sertaconazole nitrate) cream

Important information: ERTACZO cream is for use on skin only.Do not use ERTACZO cream in your eyes, mouth, or vagina.

What is ERTACZO cream?

ERTACZO cream is a prescription medicine used on the skin (topical) to treat athlete’s foot that is between the toes (interdigital tinea pedis) in adults and children 12 years of age and older with normal immune systems.

It is not known if ERTACZO cream is safe and effective in children younger than 12 years of age.

Before using ERTACZO cream, tell your healthcare provider about all of your medical conditions, including if you:

- have any allergies
- are pregnant or plan to become pregnant. It is not known if ERTACZO cream will harm your unborn baby.
- are breastfeeding or plan to breastfeed. It is not known if ERTACZO cream passes into your breast milk. Talk to your healthcare provider about the best way to feed your baby if you use ERTACZO cream.

Tell your healthcare provider about all of the medicinesyou take,including prescription and over-the-counter medicines, vitamins, and herbal supplements.

How should I use ERTACZO cream?

- Use ERTACZO cream exactly as your healthcare provider tells you to use it.
- Use ERTACZO cream for the full treatment time, even if your symptoms improve.
- If you take a bath or shower, dry the affected skin areas well before you apply ERTACZO cream.
- Apply ERTACZO cream 2 times a day for 4 weeks to the affected skin areas between your toes and to the healthy skin around the affected areas.
- Wash your hands after you apply ERTACZO cream.
- Do not cover the treated skin areas with bandages unless your healthcare provider tells you to.

What are the possible side effects of ERTACZO cream?

The most common side effects of ERTACZO cream include:redness, itching, dry skin, burning, blistering, swelling, drainage, and skin tenderness at the treated skin areas. Tell your healthcare provider if you have any of these skin reactions.

These are not all the possible side effects of ERTACZO cream.

Call your doctor for medical advice about side effects. You may report side effects to FDA at 1-800-FDA-1088.

How should I store ERTACZO cream?

- Store ERTACZO cream at room temperature between 68°F to 77°F (20°C to 25°C).
- Keep ERTACZO cream and all medicines out of reach of children.

General information about the safe and effective use of ERTACZO cream

Medicines are sometimes prescribed for purposes other than those listed in a Patient Information leaflet. Do not use ERTACZO cream for a condition for which it was not prescribed. Do not give ERTACZO cream to other people, even if they have the same symptoms you have. It may harm them. You can ask your healthcare provider or pharmacist for information about ERTACZO cream that is written for health professionals.

What are the ingredients in ERTACZO cream?

Active ingredient:sertaconazole nitrate

Inactive ingredients:ethylene glycol, glyceryl isostearate, glycolized saturated glycerides, light mineral oil, methylparaben, polyethylene glycol palmitostearate, polyoxyethylened saturated glycerides, purified water, and sorbic acid

Distributed by:
Coral Way Pharma, LLC
San Antonio, TX 78213 USA
Manufactured by:
DPT Laboratories, Ltd.
San Antonio, TX 78215
ERTACZO is a trademark of Lacer Pharma, LLC
141379

This Patient Information has been approved by the U.S. Food and Drug Administration.
Revised: 10/2025

PACKAGE/LABEL PRINCIPAL DISPLAY PANEL – 60 g Carton

NDC: 85437-004-60

ERTACZO®
(sertaconazole nitrate) cream, 2%

Rx only

For Topical Use Only - Not for Ophthalmic, Oral, or Intravaginal Use

Net Wt. 60 g